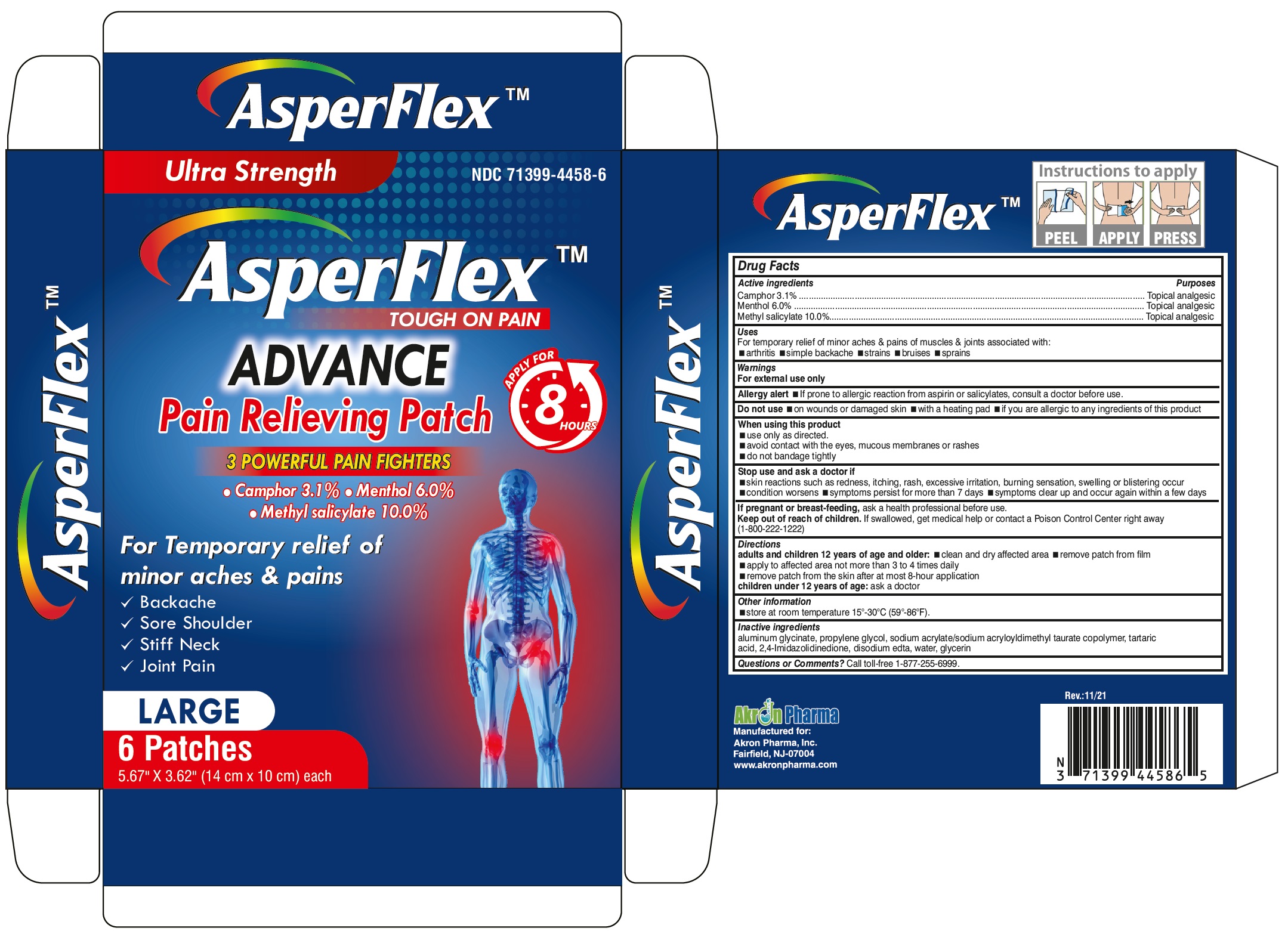 DRUG LABEL: AsperFlex Advance
NDC: 71399-4458 | Form: PATCH
Manufacturer: Akron Pharma Inc.
Category: otc | Type: HUMAN OTC DRUG LABEL
Date: 20251001

ACTIVE INGREDIENTS: CAMPHOR (SYNTHETIC) 86.24 mg/1 1; MENTHOL 166.92 mg/1 1; METHYL SALICYLATE 278.2 mg/1 1
INACTIVE INGREDIENTS: DIHYDROXYALUMINUM AMINOACETATE ANHYDROUS; PROPYLENE GLYCOL; SODIUM ACRYLATE; TARTARIC ACID; HYDANTOIN; EDETATE DISODIUM ANHYDROUS; WATER; GLYCERIN

AsperFlex
Tough on Pain
Advance Pain Relieving Patch

Active ingredients

Camphor 3.1%

Menthol 6.0%

Methyl salicylate 10.0%

Purpose

Topical analgesic

Uses

For temporary relief of minor aches and pains of muscles and joints associated with:

- arthritis
- simple backache
- strains
- bruises
- sprains

Warnings

For external use only

Allergy alert:

If prone to allergic reaction from aspirin or salicylates, consult a doctor before use.

Do not use

- on wounds or damaged skin
- with a heating pad
- if you are allergic to any ingredients of this product

When using this product

- use only as directed
- avoid contact with the eyes, mucous membranes or rashes
- do not bandage tightly

Stop use and ask a doctor if

- rash, itching or excessive skin irritation develops
- contisions worsen
- symptoms persist for more than 7 days
- symptoms clear up and occur again within a few days

If pregnant or breast-feeding,

ask a health professional before use.

Keep out of reach of children.

If swallowed, get medical help or contact a Poison Control Center right away.

Directions

Adults and children 12 years of age and over:

- clean and dry affected area
- remove patch from film
- apply to affected area not more than 3 to 4 times daily
- remove patch from the skin after at most 8-hour application

Children under 12 years of age:consult a doctor

Other information

- store at room temperature 15°-30°C (59°-86°F).

Inactive ingredients

aluminum glycinate, propylene glycol, sodium acrylate/sodium acryloyldimethyl taurate copolymer, tartaric acid, 2,4-Imidazolidinedione, disodium edta, water, glycerin

Questions or comments?

Call toll-free 1-877-255-6999.

Manufactured for:
Akron Pharma, Inc.
Fairfield, NJ 07004

www.akronpharma.com